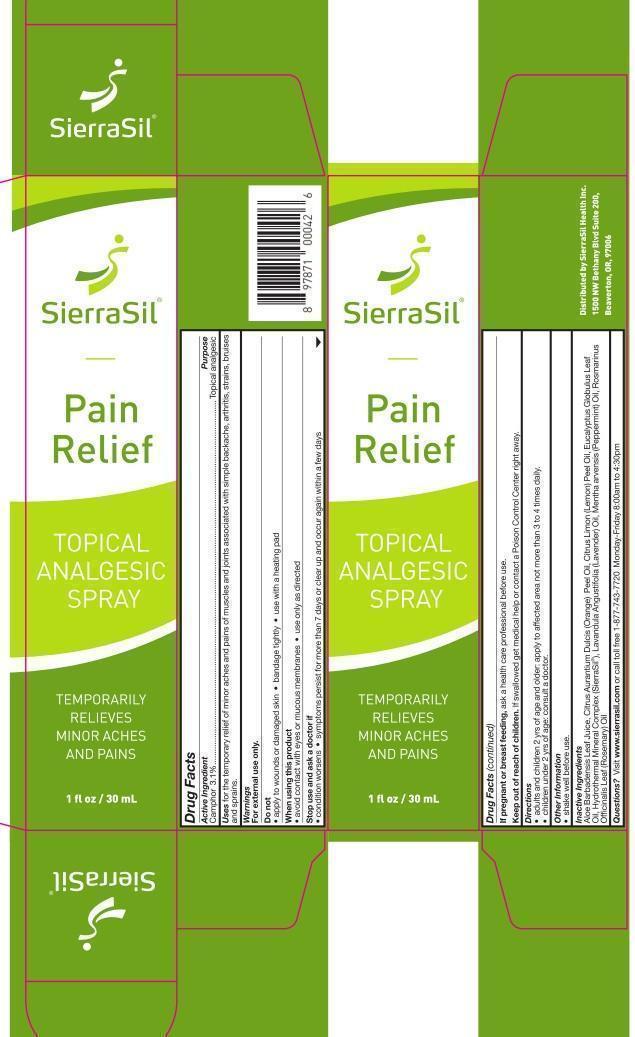 DRUG LABEL: SierraSil Pain Relief
NDC: 72608-002 | Form: SPRAY
Manufacturer: D&d Essential Oils, Llc.
Category: otc | Type: HUMAN OTC DRUG LABEL
Date: 20181014

ACTIVE INGREDIENTS: CAMPHOR (NATURAL) 3.1 g/100 mL
INACTIVE INGREDIENTS: ALOE VERA LEAF; ORANGE OIL; LEMON OIL; EUCALYPTUS OIL; LAVENDER OIL; MENTHA ARVENSIS FLOWER OIL; ROSEMARY OIL

Drug Facts

Active Ingredient

Camphor 3.1%

Purpose

Camphor 3.1%.........................................Topical analgesic

Uses

for the temporary relief of minor aches and pains of muscles and joints associated with simple backache, arthritis, strains, bruises and sprains.

Warnings

For external use only.

Do not

- apply to wounds or damaged skin
- bandage tightly
- use with a heating pad

When using this product

- avoid contact with eyes or mucous membranes
- use only as directed

Stop use and ask a doctor if

- condition worsens
- symptoms persist for more than 7 days or clear up and occur again within a few days

PREGNANCY OR BREAST FEEDING

If pregnant or breast feeding, ask a health care professional before use.

Keep out of reach of children.

OTHER SAFETY INFORMATION

If swallowed get medical help or contact a Poison Control Center right away.

Directions

- adults and children 2 yrs of age and older: apply to affected area not more than 3 to 4 times daily.
- children under 2 yrs of age: consult a doctor.

Other Information

- shake well before use.

Inactive Ingredients

Aloe Barbadensis Leaf Juice, Citrus Aurantium Dulcis (Orange) Peel Oil, Citrus Limon (Lemon) Peel Oil, Eucalyptus Globulus Leaf Oil, Hydrothermal Mineral Complex (SierraSil), Lavandula Angustifolia (Lavender) Oil, Mentha arvensis (Peppermint) Oil, Rosmarinus Officinalis Leaf (Rosemary) Oil

Questions?

Visit www.sierrasil.com or call toll free 1-877-743-7720 Monday-Friday 8:00am to 4:30pm

DESCRIPTION

Distributed by SierraSil Health Inc.

1500 NW Bethany Blvd Suite 200,

Beaverton, OR, 97006

Principal Display Panel

SierraSil

Pain

Relief

TOPICAL

ANALGESIC

SPRAY

TEMPORARILY

RELIEVES

MINOR ACHES

AND PAINS

1 fl oz / 30 mL